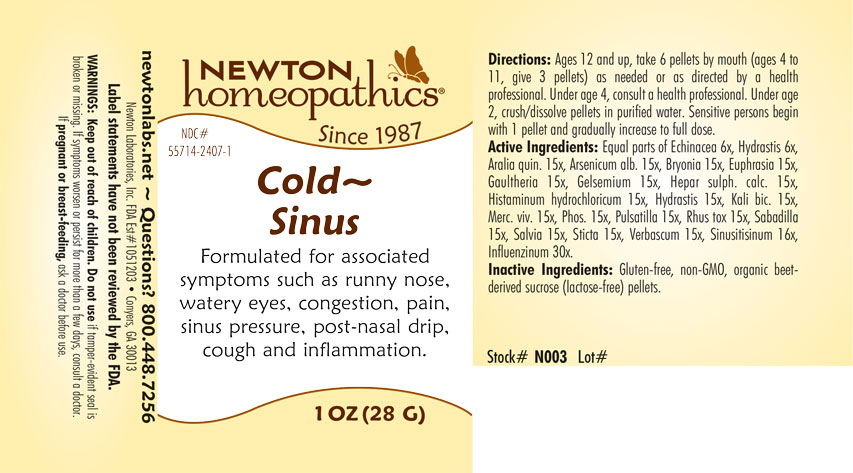 DRUG LABEL: Cold - Sinus
NDC: 55714-2407 | Form: PELLET
Manufacturer: Newton Laboratories, Inc.
Category: homeopathic | Type: HUMAN OTC DRUG LABEL
Date: 20220317

ACTIVE INGREDIENTS: INFLUENZA A VIRUS 30 [hp_X]/1 g; AMERICAN GINSENG 15 [hp_X]/1 g; ARSENIC TRIOXIDE 15 [hp_C]/1 g; BRYONIA ALBA ROOT 15 [hp_X]/1 g; EUPHRASIA STRICTA 15 [hp_X]/1 g; GAULTHERIA PROCUMBENS TOP 15 [hp_X]/1 g; GELSEMIUM SEMPERVIRENS ROOT 15 [hp_X]/1 g; CALCIUM SULFIDE 15 [hp_X]/1 g; HISTAMINE DIHYDROCHLORIDE 15 [hp_X]/1 g; GOLDENSEAL 15 [hp_X]/1 g; POTASSIUM DICHROMATE 15 [hp_X]/1 g; MERCURY 15 [hp_X]/1 g; PHOSPHORUS 15 [hp_X]/1 g; PULSATILLA VULGARIS 15 [hp_X]/1 g; TOXICODENDRON PUBESCENS LEAF 15 [hp_X]/1 g; SCHOENOCAULON OFFICINALE SEED 15 [hp_X]/1 g; SAGE 15 [hp_X]/1 g; LOBARIA PULMONARIA 15 [hp_X]/1 g; VERBASCUM THAPSUS 15 [hp_X]/1 g; ECHINACEA, UNSPECIFIED 6 [hp_X]/1 g; INFLUENZA B VIRUS 30 [hp_X]/1 g; SINUSITISINUM 16 [hp_X]/1 g
INACTIVE INGREDIENTS: SUCROSE

ColdSi 2407P

WARNINGS SECTION

WARNING: Keep out of reach of children. Do not use if tamper-evident seal is broken or missing. If symptoms persist for more than a few days, consult a doctor. If pregnant or breast-feeding, ask a doctor before use.

OTC - KEEP OUT OF REACH OF CHILDREN SECTION

Keep out of reach of children.

OTC - PREGNANCY OR BREAST FEEDING SECTION

If pregnant or breast-feeding, ask a doctor before use.

QUESTIONS SECTION

newtonlabs.net - Questions? 800.448.7256

Newtton Laboratories, Inc. FDA Est # 1051203 - Conyers, GA 30013

INACTIVE INGREDIENT SECTION

Gluten-free, non-GMO, organic beet-derived sucrose (lactose-free) pellets.

OTC - PURPOSE SECTION

Formulated for associated symptoms such as runny nose, watery eyes, congestion, pain, sinus pressure, post-nasal drip, cough and inflammation.

OTC - ACTIVE INGREDENT SECTION

Equal parts of Echinacea 6x, Hydrastis 6x, Aralia quin. 15x, Arsenicum alb. 15x, Bryonia 15x, Euphrasia 15x, Gaultheria 15x, Gelsemium 15x, Hepar sulph. calc. 15x, Histaminum hydrochloricum 15x, Hydrastis 15x, Kali bic. 15x, Merc. viv. 15x, Phos. 15x, Pulsatilla 15x, Rhus tox. 15x, Sabadilla 15x, Salvia 15x, Sticta 15x, Verbascum 15x, Sinusitisinum 16x, Influenzinum 30x.

DOSAGE & ADMINISTRATION SECTION

Ages 12 and up, take 6 pellets by mouth (ages 4 to 11, give 3 pellets) as needed or as directed by a health professional. Under age 4 consult a health professional. Under age 2, crush or dissolve pellets in purfied water. Sensitive persons begin with 1 pellet and gradually increase to full dose.

INDICATIONS & USAGE SECTION

Formulated for associated symptoms such as runny nose, watery eyes, congestion, pain, sinus pressure, post-nasal drip, cough and inflammation.